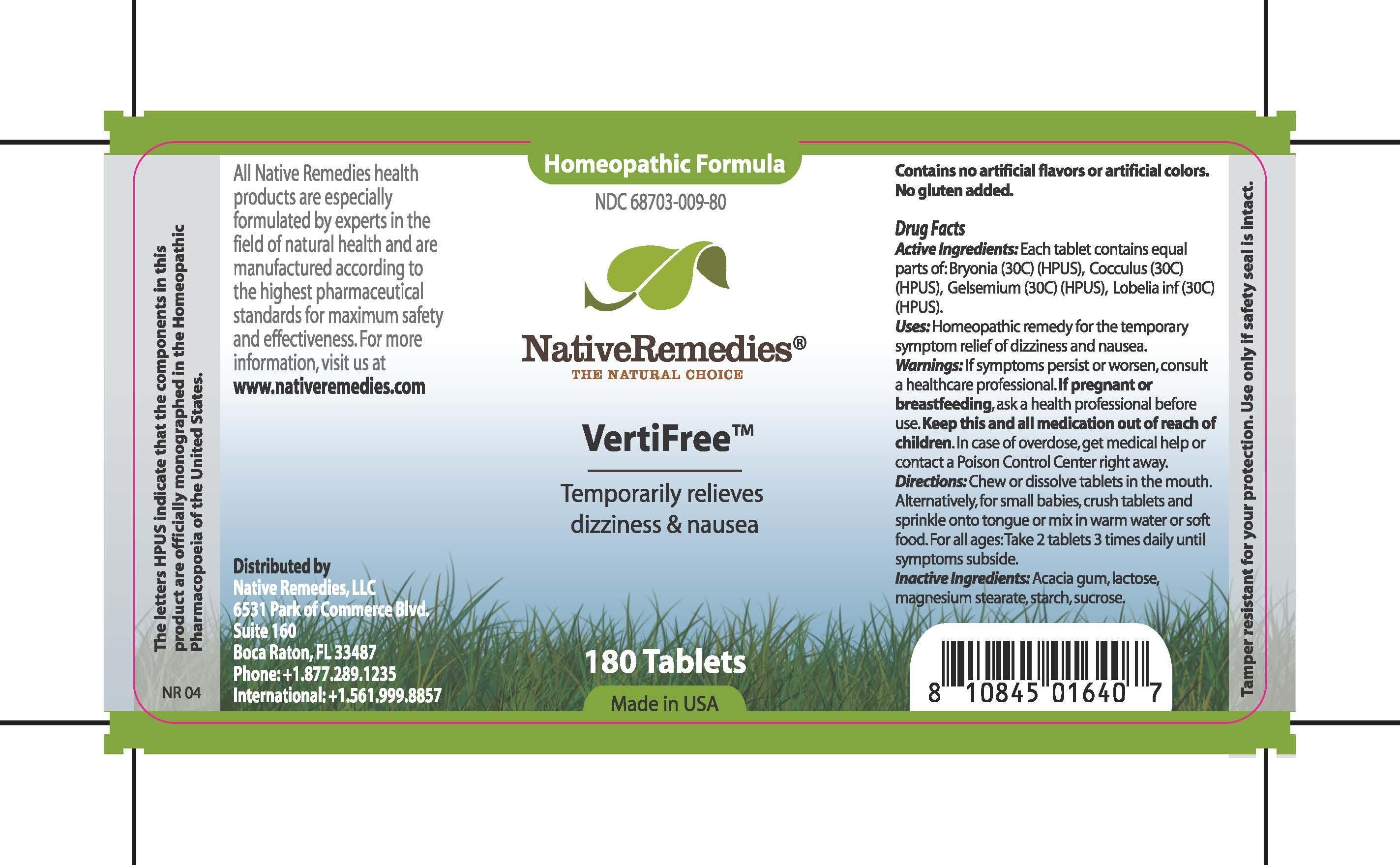 DRUG LABEL: VertiFree
NDC: 68703-009 | Form: TABLET
Manufacturer: Native Remedies LLC
Category: homeopathic | Type: HUMAN OTC DRUG LABEL
Date: 20121129

ACTIVE INGREDIENTS: BRYONIA ALBA ROOT 30 [hp_C]/1 1; ANAMIRTA COCCULUS SEED 30 [hp_C]/1 1; GELSEMIUM SEMPERVIRENS ROOT 30 [hp_C]/1 1; LOBELIA INFLATA 30 [hp_C]/1 1
INACTIVE INGREDIENTS: ACACIA; LACTOSE; MAGNESIUM STEARATE; STARCH, CORN; SUCROSE

VertiFree

PURPOSE

Temporarily relieves dizziness and nausea

ACTIVE INGREDIENT

Active Ingredients: Each tablet contains equal parts of: Bryonia (30C) (HPUS), Cocculus (30C) (HPUS), Gelsemium (30C) (HPUS), Lobelia inf (30C) (HPUS).

INDICATIONS AND USAGE

Uses: Homeopathic remedy for the temporary symptom relief of dizziness and nausea.

WARNINGS

Warnings: If symptoms persist or worsen, consult a healthcare professional.

PREGNANCY OR BREAST FEEDING

If pregnant or breastfeeding, ask a health professional before use.

KEEP OUT OF REACH OF CHILDREN

Keep this and all medication out of reach of children.

OVERDOSAGE

In case of overdose, get medical help or contact a Poison Control Center right away.

DOSAGE AND ADMINISTRATION

Directions: Chew or dissolve tablets in the mouth.Alternatively, for small babies, crush tablets and sprinkle onto tongue or mix in warm water or soft food.For all ages: Takes 2 tablets 3 times daily until symptoms subside.

INACTIVE INGREDIENT

Inactive Ingredients: Acacia gum, lactose, magnesium stearate, starch, sucrose.

PATIENT COUNSELING INFORMATION

The letters HPUS indicate that the components in this products are officially monographed in the Homeopathic Pharmacopoeia of the United States.

All Native Remedies health products are especially formulated by experts in the field of natural health and are manufactured according to the highest pharmaceutical standards for maximum safety and effectiveness. For more information, visit us at www.nativeremedies.com
Distributed by
Native Remedies, LLC
6531 Park of Commerce Blvd.
Suite 160
Boca Raton, FL 33487
Phone: +1.877.289.1235
International:+1.561.99.8857
Contains no artificial flavors or artificial colors. No gluten added.

STORAGE AND HANDLING

Tamper resistant for your protection. Use only if safety seal is intact.